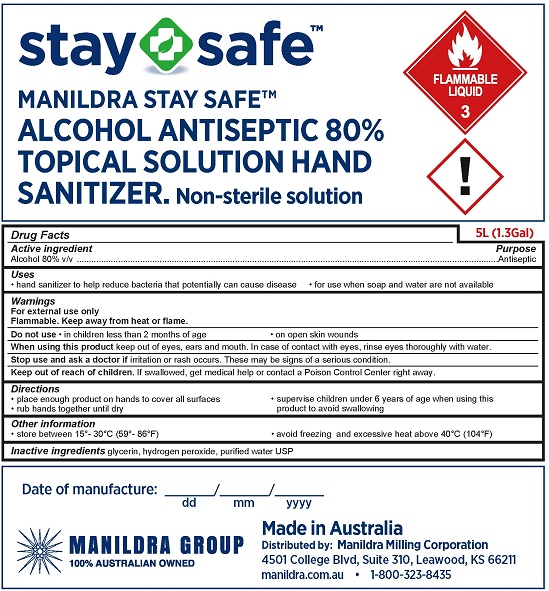 DRUG LABEL: Manildra Stay Safe
NDC: 79268-001 | Form: LIQUID
Manufacturer: Manildra Milling Coporation
Category: otc | Type: HUMAN OTC DRUG LABEL
Date: 20200724

ACTIVE INGREDIENTS: ALCOHOL 80 L/100 L
INACTIVE INGREDIENTS: HYDROGEN PEROXIDE; WATER; GLYCERIN

Manildra Stay Safe Alcohol 80% Hand Sanitizer

Drug Facts

Active ingredient

Alcohol 80% v/v

Purpose
Antiseptic

Uses

- hand sanitizer to help reduce bacteria that potentially can cause disease
- for use when soap and water are not available

Warnings
For external use only.

Flammable. Keep away from heat or flame.

Do not use

- in children less than 2 months of age
- on open skin wounds

When using this product keep out of eyes, ears and mouth. In case of contact with eyes, rinse eyes thoroughly with water.

Stop use and ask a doctor if irritation or rash occurs. These may be signs of a serious condition.

Keep out of reach of children. If swallowed, get medical help or contact a Poison Control Center immediately.

Directions

- place enough product on hands to cover all surfaces
- rub hands together until dry
- supervise children under 6 years of age when using this product to avoid swallowing

Inactive ingredients

glycerin, hydrogen peroxide, purified water USP

MANILDRA GROUP

100% AUSTRALIAN OWNED

Made in Australia

Distributed by: Manildra Milling Corporation
4501 College Blvd, Suite 310, Leawood, KS 66211

manildra.com.au • 1-800-323-8435

PACKAGE LABEL

stay safe™
MANILDRA STAY SAFE™
ALCOHOL ANTISEPTIC 80%
TOPICAL SOLUTION HAND SANITIZER.
Non-Sterile Solution
FLAMMABLE LIQUID
5L (1.3 Gal)